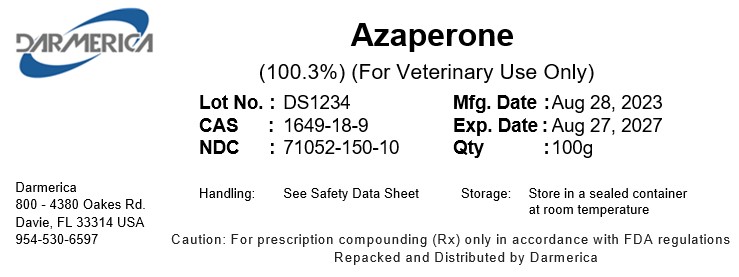 DRUG LABEL: Azaperone
NDC: 71052-150 | Form: POWDER
Manufacturer: DARMERICA, LLC
Category: other | Type: BULK INGREDIENT - ANIMAL DRUG
Date: 20250108

ACTIVE INGREDIENTS: AZAPERONE 1 kg/1 kg

AZAPERONE